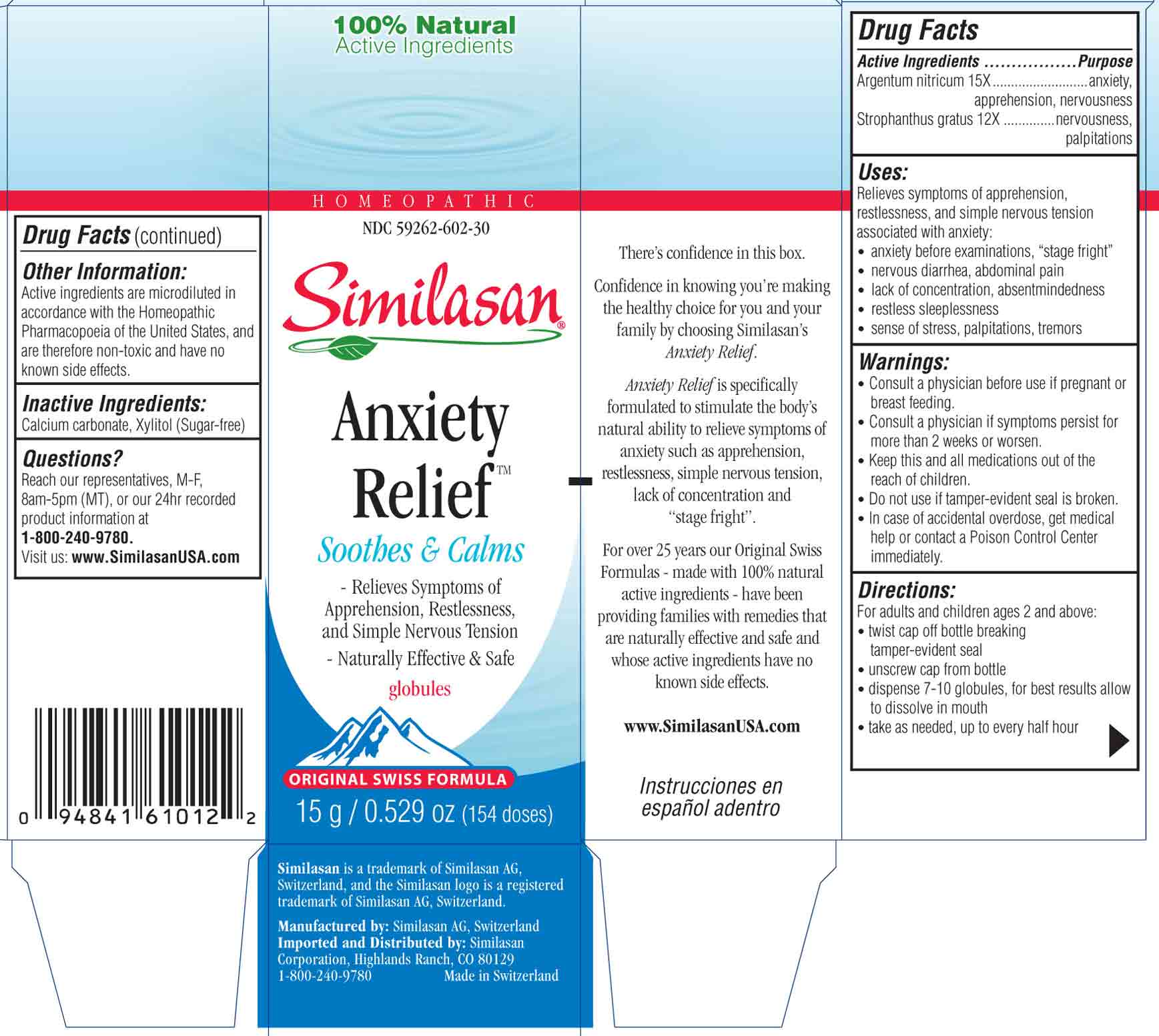 DRUG LABEL: Anxiety Relief
NDC: 59262-602 | Form: GLOBULE
Manufacturer: Similasan Corporation
Category: homeopathic | Type: HUMAN OTC DRUG LABEL
Date: 20130815

ACTIVE INGREDIENTS: SILVER NITRATE 15 [hp_X]/1 1; STROPHANTHUS GRATUS SEED 12 [hp_X]/1 1
INACTIVE INGREDIENTS: CALCIUM CARBONATE; XYLITOL

Anxiety Relief

Active ingredient(s)

Argentum nitricum 15X

Purpose

anxiety, apprehension, nervousness

Active ingredient(s)

Strophantus gratus 12X

Purpose

nervousness, palpitations

Uses:

Relieves symptoms of apprehension, restlessness, and simple nervous tension associated with anxiety:
- anxiety before examinations, "stage fright"
- nervous diarrhea, abdominal pain
- lack of concentration, absentmindedness
- restless sleeplessness
- sense of stress, palpitations, tremors

Warnings:

- Consult a physician before use if pregnant or breast feeding.
- Consult a physician if symptoms persist for more than 2 weeks or worsen.
- Keep this and all medications out of the reach of children.
- Do not use if tamper-evident seal is broken.
- In case of accidental overdose, get medical help or contact a Poison Control Center immediately.

Keep out of reach of children

Keep this and all medications out of the reach of children

Directions:

For adults and children ages 2 and above:
- twist cap off bottle breaking tamper-evident seal
- unscrew cap from bottle
- dispense 7-10 globules, place in mouth and allow to dissolve.
- take as needed up to every half hour.

Other information:

Active ingredients are microdiluted in accordance with the Homeopathic Pharmacopoeia of the United States, and are therefore non-toxic and have no known side effects.

Inactive ingredients:

Calcium carbonate, Xylitol (Sugar-free)

Questions?

Reach our representatvies, M-F, 8am-5pm (MT), or our 24 hr recorded product information at 1-800-240-9780. Visit us: www.SimilasanUSA.com.

Principal Display Panel

NDC 59262-602-30
Similasan
Anxiety Relief
Globules
15g/ 0.529 oz

Anxiety Relief box